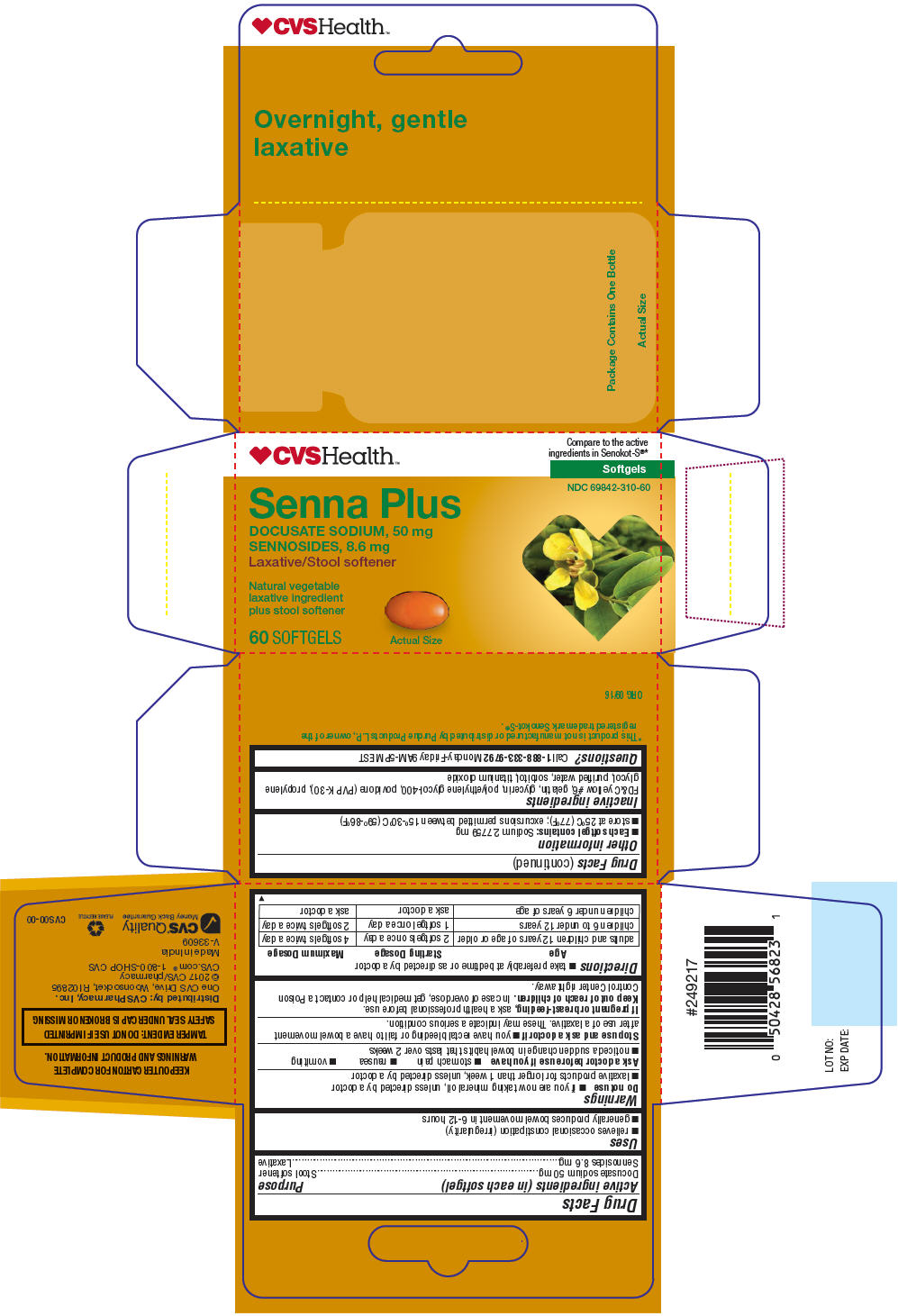 DRUG LABEL: SENNA-S
NDC: 69842-310 | Form: CAPSULE, GELATIN COATED
Manufacturer: CVS
Category: otc | Type: HUMAN OTC DRUG LABEL
Date: 20241217

ACTIVE INGREDIENTS: DOCUSATE SODIUM 50 mg/1 1; SENNOSIDES 8.6 mg/1 1
INACTIVE INGREDIENTS: FD&C YELLOW NO. 6; GELATIN, UNSPECIFIED; GLYCERIN; POLYETHYLENE GLYCOL 400; POVIDONE K30; PROPYLENE GLYCOL; WATER; SORBITOL; TITANIUM DIOXIDE

SENNA-S

Drug Facts

ACTIVE INGREDIENT

Active ingredients (in each softgel) | Purpose
Docusate sodium 50 mg | Stool softener
Sennosides 8.6 mg | Laxative

Uses

- relieves occasional constipation (irregularity)
- generally produces bowel movement in 6-12 hours

Warnings

Do not use

- if you are now taking mineral oil, unless directed by a doctor
- laxative products for longer than 1 week, unless directed by a doctor

Ask a doctor before use if you have

- stomach pain
- nausea
- vomiting
- noticed a sudden change in bowel habits that lasts over 2 weeks

Stop use and ask a doctor if

- you have rectal bleeding or fail to have a bowel movement after use of a laxative. These may indicate a serious condition.

PREGNANCY OR BREAST FEEDING

If pregnant or breast-feeding, ask a health professional before use.

Keep out of reach of children. In case of overdose, get medical help or contact a Poison Control Center right away.

Directions

- take preferably at bedtime or as directed by a doctor

Age | Starting Dosage | Maximum Dosage
adults and children 12 years of age or older | 2 softgels once a day | 4 softgels twice a day
children 6 to under 12 years | 1 softgel once a day | 2 softgels twice a day
children under 6 years of age | ask a doctor | ask a doctor

Other information

- Each softgel contains: Sodium 2.7759 mg
- store at 25°C (77°F); excursions permitted between 15°-30°C (59°-86°F)

Inactive ingredients

FD&C yellow #6, gelatin, glycerin, polyethylene glycol-400, povidone (PVP K-30), propylene glycol, purified water, sorbitol, titanium dioxide

Questions?

Call 1-888-333-9792 Monday-Friday 9AM-5PM EST

Distributed by: CVS Pharmacy, Inc.
One CVS Drive, Woonsocket, RI 02895

PRINCIPAL DISPLAY PANEL - 60 Capsule Bottle Carton

♥CVSHealth™

Compare to the active
ingredients in Senokot-S®*

Softgels

NDC 69842-310-60

Senna Plus
DOCUSATE SODIUM, 50 mg
SENNOSIDES, 8.6 mg
Laxative/Stool softener

Natural vegetable
laxative ingredient
plus stool softener

60 SOFTGELS

Actual Size